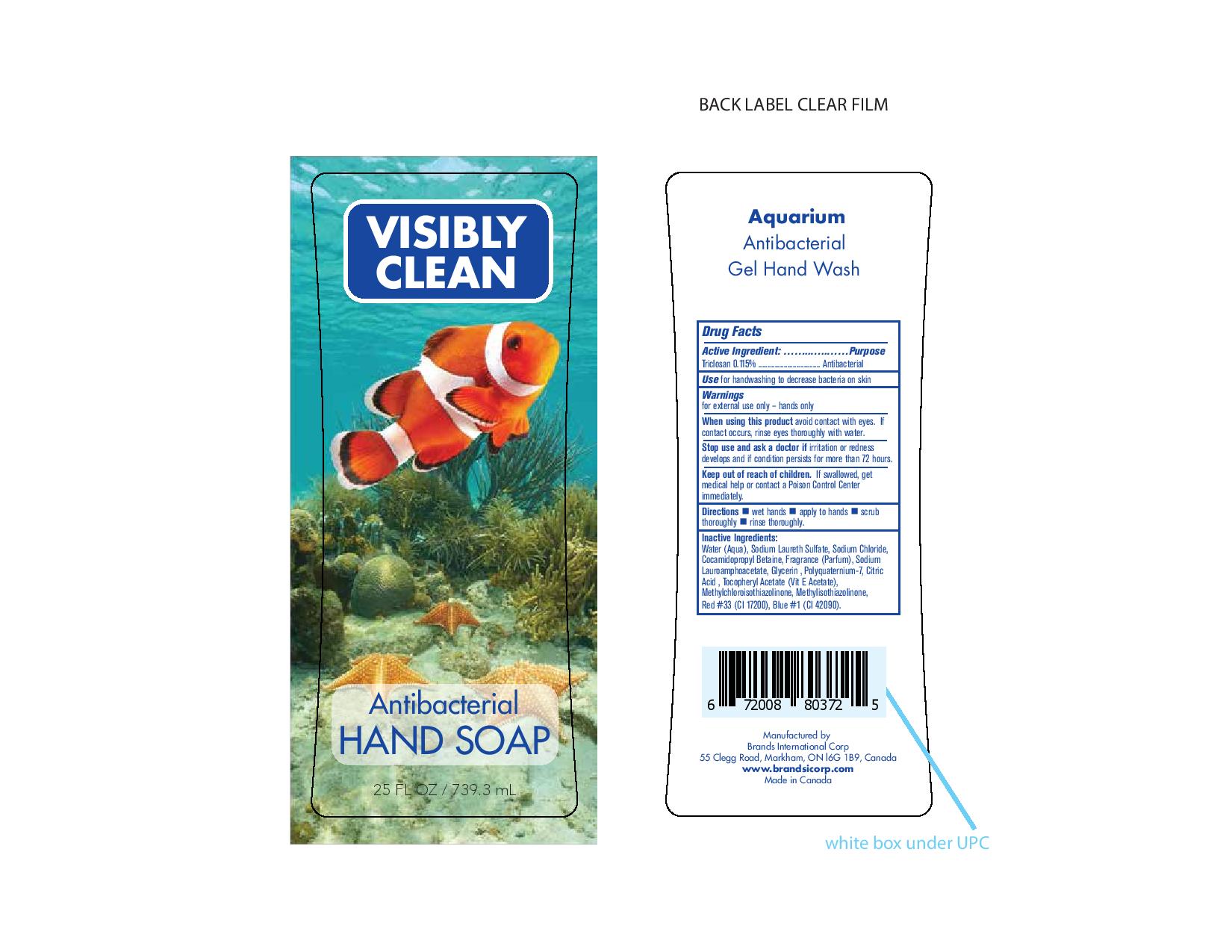 DRUG LABEL: Antibacterial
NDC: 50157-202 | Form: LIQUID
Manufacturer: Brands International Corp
Category: otc | Type: HUMAN OTC DRUG LABEL
Date: 20161023

ACTIVE INGREDIENTS: TRICLOSAN 1.15 mg/1 mL
INACTIVE INGREDIENTS: WATER; METHYLCHLOROISOTHIAZOLINONE; SODIUM LAURETH SULFATE; SODIUM CHLORIDE; COCAMIDOPROPYL BETAINE; SODIUM LAUROAMPHOACETATE; GLYCERIN; POLYQUATERNIUM-7 (70/30 ACRYLAMIDE/DADMAC; 1600 KD); ANHYDROUS CITRIC ACID; .ALPHA.-TOCOPHEROL ACETATE; METHYLISOTHIAZOLINONE; D&C RED NO. 33; FD&C BLUE NO. 1

Active Ingredient - Triclosan 0.115%

purpose - antibacterial

INDICATIONS AND USAGE

Use for handwashing to decrease bacteria on skin

Warning

for extrenal use only - hands only

When using this product avoid contact with eyes. If contact occurs, rinse eyes thoroughly with water

Stop use and ask a doctor If irritation or redness develops and if condition persists for more than 72 hours

Keep out of reach of children. If swallowed, get medical help or contact a Poison Control Center immediately

DOSAGE AND ADMINISTRATION

Direction

- Wet hands
- apply to hands
- scrub thoroughly
- rinse thoroughly

INACTIVE INGREDIENT

Water (Aqua), Sodium Laureth Sulfate, Sodium Chloride, Cocamidopropyl Betaine, Fragrance (Parfum), Sodium Lauroamphacetate, Glycerin, Polyquaternium - 7, Citric Acid, Tocopheryl Acetate, (Vit E Acetate), Methylchloroisothiazolinone, Methylisothiazolinone, Red 33 (Cl 17200), Blue 1 (42090)